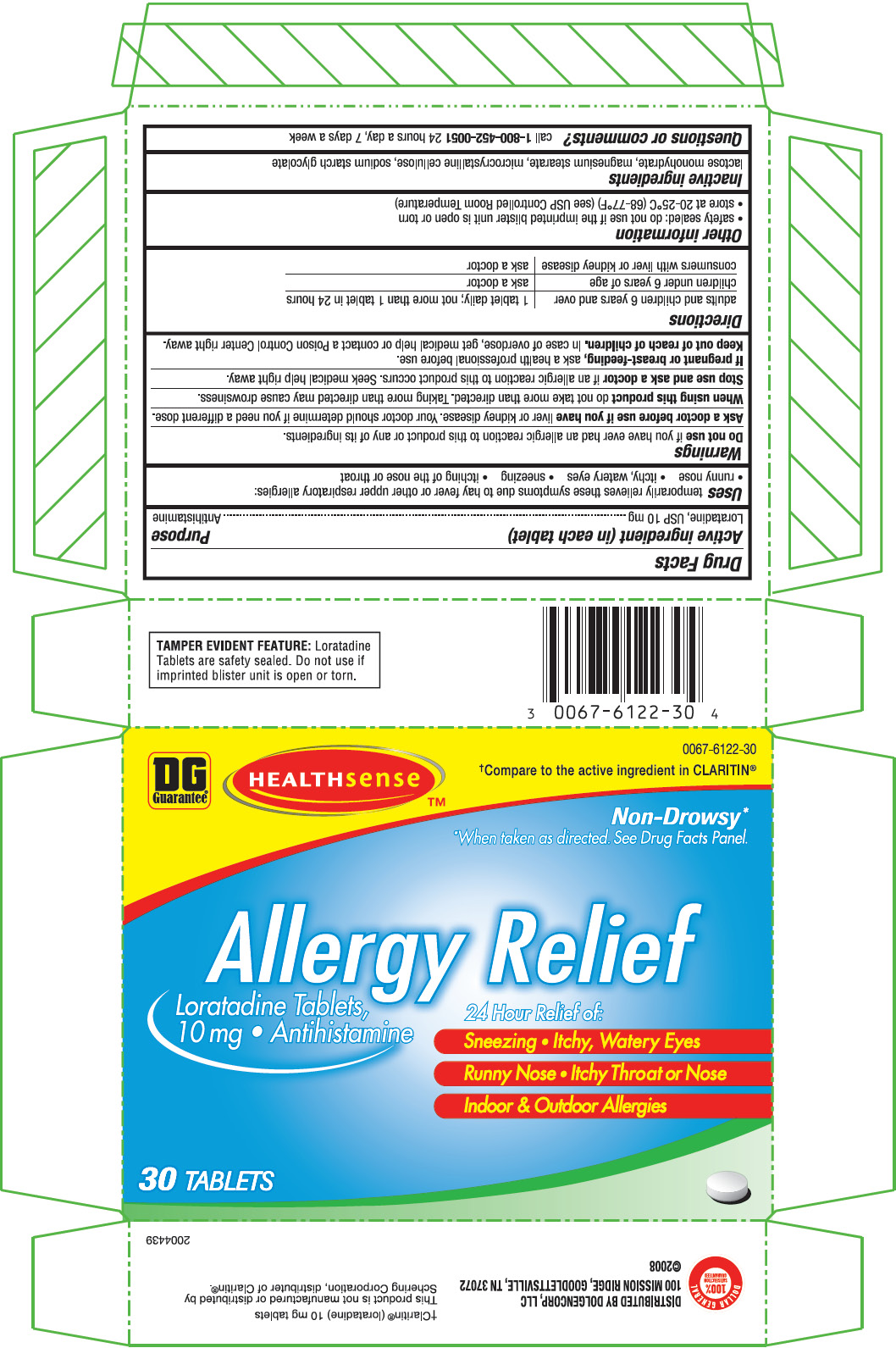 DRUG LABEL: allergy relief
NDC: 0067-6122 | Form: TABLET
Manufacturer: Novartsi Consumer Health, Inc.
Category: otc | Type: HUMAN OTC DRUG LABEL
Date: 20091201

ACTIVE INGREDIENTS: LORATADINE 10 mg/1 1
INACTIVE INGREDIENTS: CELLULOSE, MICROCRYSTALLINE; LACTOSE MONOHYDRATE; MAGNESIUM STEARATE; SODIUM STARCH GLYCOLATE TYPE A POTATO

Drug Facts

Active ingredient

loratadine 10mg

Purpose

antihistamine

Uses

temporarily relieves these symptoms due to hay fever or other upper respiratory allergies:

• runny nose • itchy, watery eyes • sneezing • itching of the nose or throat

Do not use if you have ever had an allergic reaction to this product or any of its ingredients.

Ask Doctor

Ask a doctor before use if you have liver or kidney disease. Your doctor should determine if you need a different dose.

When Using

When using this product do not take more than directed. Taking more than directed may cause drowsiness.

Stop Use

Stop use and ask a doctor if an allergic reaction to this product occurs. Seek medical help right away.

Pregnancy or Breast Feeding

If pregnant or breast-feeding, ask a health professional before use.

Keep Out of Reach of Children

Overdose

In case of overdose, get medical help or contact a Poison Control Center right away.

Other Information

- safety sealed: do not use if the imprinted bottle seal with “sealed for your protection” is open or torn (for bottle carton only)
- safety sealed: do not use if the imprinted blister unit is open or torn (for blister carton only)
- store at 20-25°C (68-77°F) (see USP Controlled Room Temperature)

Directions

adults and children 6 years and over | 1 tablet daily; not more than 1 tablet in 24 hours
children under 6 years of age | ask a doctor
consumers with liver or kidney disease | ask a doctor

Inactive ingredients

lactose monohydrate, magnesium stearate, microcrystalline cellulose, sodium starch glycolate

Questions

call 1-800-452-0051

Distributed by DOLGENCORP, LLC

100 Mission Ridge

Goodlettsville, TN 37072

Principal Display

Dollar General